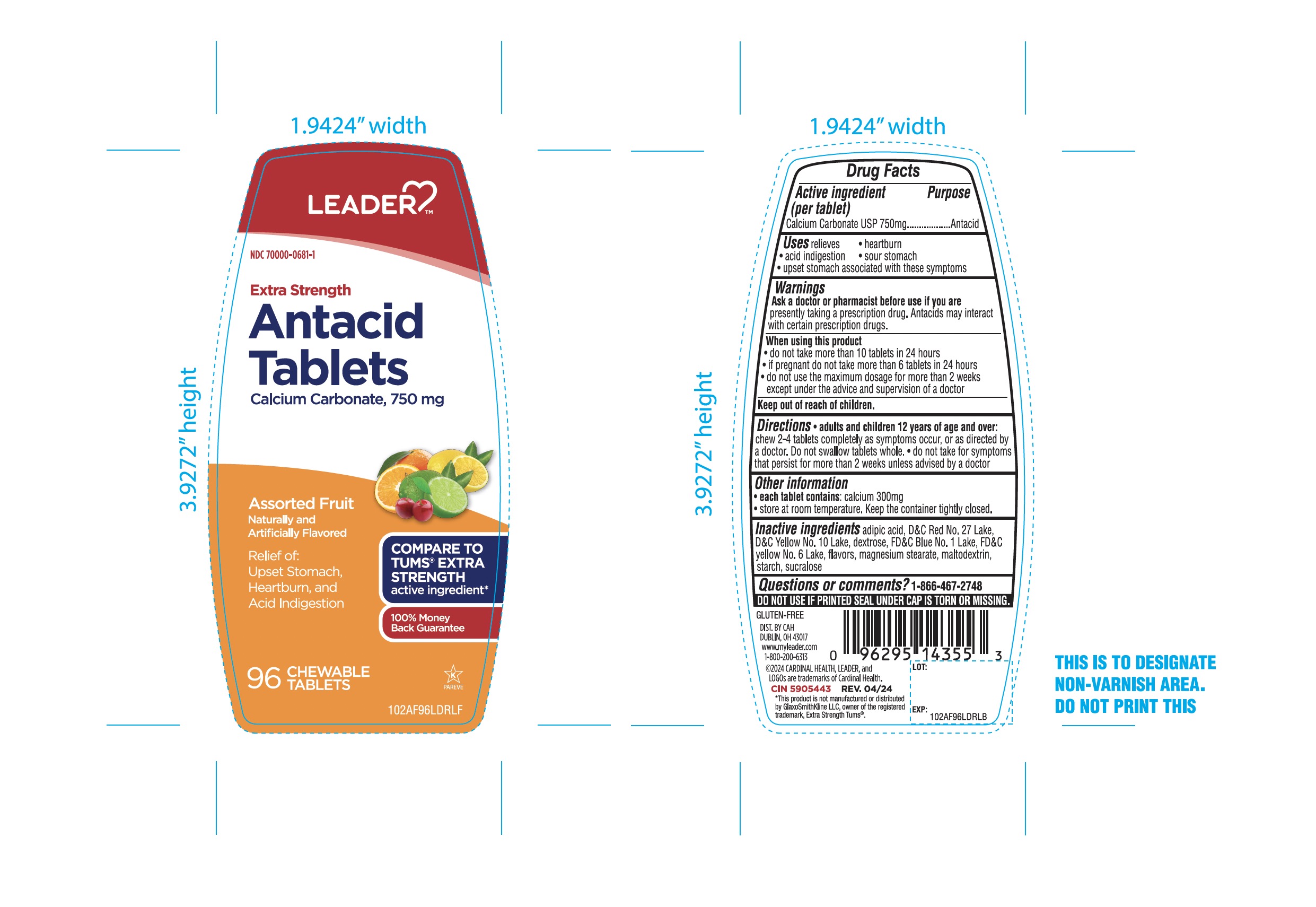 DRUG LABEL: ANTACID

NDC: 70000-0681 | Form: TABLET, CHEWABLE
Manufacturer: Cardinal Health 110, LLC.
Category: otc | Type: HUMAN OTC DRUG LABEL
Date: 20251014

ACTIVE INGREDIENTS: CALCIUM CARBONATE 750 mg/1 1
INACTIVE INGREDIENTS: ADIPIC ACID; D&C RED NO. 27; D&C YELLOW NO. 10; DEXTROSE, UNSPECIFIED FORM; FD&C BLUE NO. 1; FD&C YELLOW NO. 6; MAGNESIUM STEARATE; MALTODEXTRIN; STARCH, CORN; SUCRALOSE

Cardinal Health Extra Strength Antacid Tablets Drug Facts

Active ingredient (in each tablet)

Calcium carbonate 750 mg

Purpose

Antacid

Uses

relieves

- heartburn
- sour stomach
- acid indigestion
- upset stomach associated with this symptom

Warnings

Ask a doctor or pharmacist before use if you are

- taking a prescription drug. Antacids may interact with certain prescription drugs.

When using this product

- do not take more than 10 tablets in 24 hours
- If pregnant do not take more than 6 tablets in 24 hours
- do not use the maximum dosage for more than 2 weeks except under the advice and supervision of a doctor

Directions

- adults and children 12 years of age and over:Chew 2-4 tablets completely as symptoms occur, or as directed by a doctor. Do not swallow tablets whole
- Do not take for symptoms that persist for more than 2 weeks unless advised by a doctor

Other information

- Each tablet contains: calcium 300mg
- Store at room temperature
- Keep the container tightly closed.

Inactive ingredients

adipic acid, D&C Red No. 27 Lake, D&C Yellow No. 10 Lake, dextrose, FD&C Blue No. 1 Lake, FD&C Yellow No. 6 Lake, Flavors, magnesium stearate, maltodextrin, starch, sucralose,

Questions?

1-866-467-2748

Principal Display Panel

LEADER™

NDC 70000-0681-1

COMPARE TO TUMS® EXTRA STRENGTH active ingredient*

Extra Strength

Antacid Tablets

Calcium Carbonate 750 mg

Assorted Fruit Flavors

Naturally and Artificially Flavored

Relief of:

- Upset Stomach
- Heartburn, and
- Acid Indigestion

100% Money Back Guarantee

96 CHEWABLE TABLETS

DO NOT USE IF PRINTED SEAL UNDER CAP IS TORN OR MISSING.

GLUTEN-FREE

Distributed BY: CAH

Dublin, Ohio 43017

www.myleader.com

1-800-200-6313

CIN 5905443

*This product is not manufactured or distributed by GlaxoSmithKline LLC, owner of the registered trademark, Extra Strength Tums®.